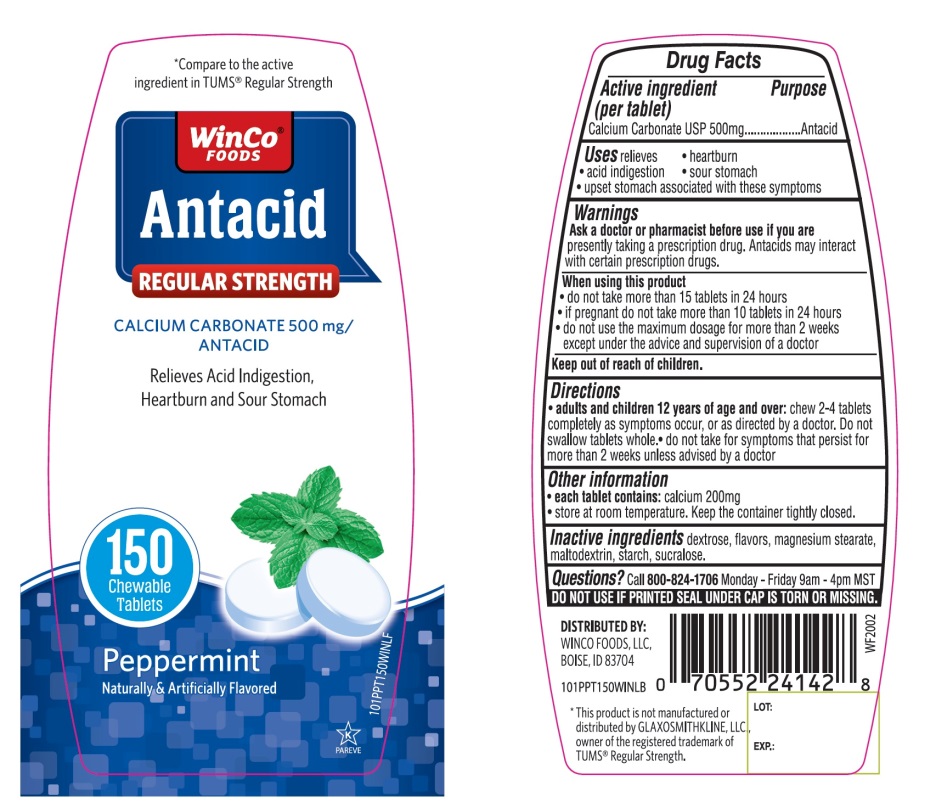 DRUG LABEL: WinCo FOODS Antacid

NDC: 67091-357 | Form: TABLET, CHEWABLE
Manufacturer: WINCO FOODS, LLC
Category: otc | Type: HUMAN OTC DRUG LABEL
Date: 20251202

ACTIVE INGREDIENTS: CALCIUM CARBONATE 500 mg/1 1
INACTIVE INGREDIENTS: DEXTROSE, UNSPECIFIED FORM; MAGNESIUM STEARATE; MALTODEXTRIN; STARCH, CORN; SUCRALOSE

WinCo® FOODS Antacid Regular Strength Peppermint Flavor Antacid Drug Facts

Active ingredient (per tablet)

Calcium Carbonate USP 500mg

Purpose

Antacid

Uses

relieves

- heartburn
- acid indigestion
- sour stomach
- upset stomach associated with these symptoms

Warnings

Ask a doctor or pharmacist before use if you are

presently taking a prescription drug. Antacids may interact with certain prescription drugs.

When using this product

- do not take more than 15 tablets in 24 hours
- if pregnant do not take more than 10 tablets in 24 hours
- do not use the maximum dosage for more than 2 weeks except under the advice and supervision of a doctor

Directions

- adults and children 12 years of age and over:chew 2-4 tablets as symptoms occur, or as directed by a doctor. Do not swallow tablets whole.
- do not take for symptoms that persist for more than 2 weeks unless advised by a doctor

Other information

- each tablet contains: elemental calcium 200mg
- store at room temperature. Keep the container tightly closed.

Inactive ingredients

dextrose, flavor, magnesium stearate, maltodextrin, starch, sucralose.

Questions?

Call 1-800-824-1706

SAFETY SEALED:DO NOT USE IF PRINTED SEAL UNDER CAP IS TORN OR MISSING.

Principal Display Panel

WinCo®FOODS

NDC#67091-357-15

Compare to the active ingredient in TUMS®Regular Strength

Antacid

REGULAR STRENGTH

CALCIUM CARBONATE 500mg/ANTACID

Fast Relief of Acid Indigestion, Heartburn and Upset Stomach

Peppermint

Naturally and Artificially Flavored

150 CHEWABLE TABLETS

GLUTEN FREE

K PAREVE

DISTRIBUTED BY:WINCO FOODS, LLC

BOISE, ID 83704

*This product is not manufactured or distributed by GLAXOSMITHKLINE LLC, owner of the registered trademark, Tums®Regular Strength.